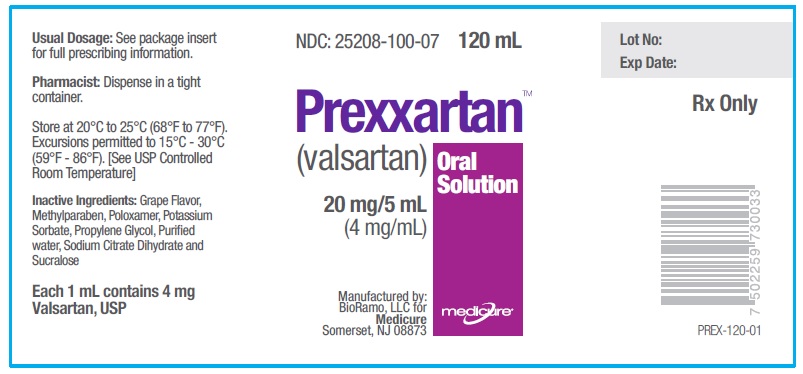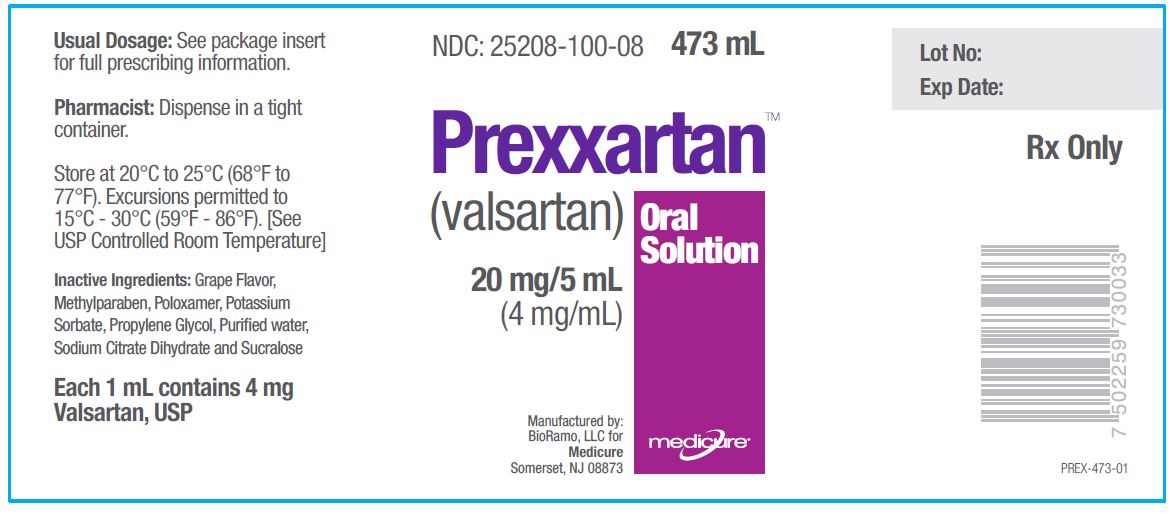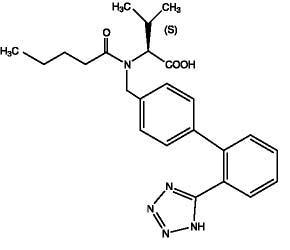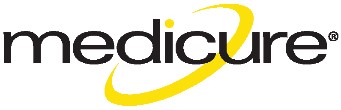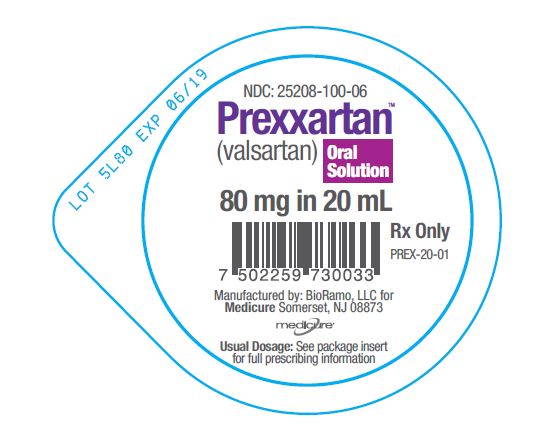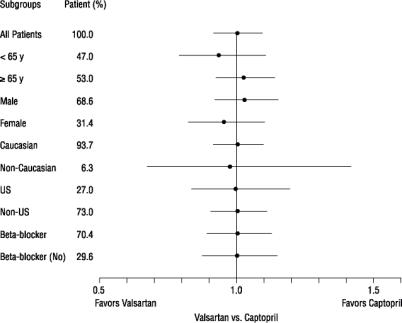 DRUG LABEL: PREXXARTAN
NDC: 25208-100 | Form: SOLUTION
Manufacturer: Medicure International Inc.
Category: prescription | Type: HUMAN PRESCRIPTION DRUG LABEL
Date: 20180102

ACTIVE INGREDIENTS: VALSARTAN 4 mg/1 mL
INACTIVE INGREDIENTS: METHYLPARABEN; POLOXAMER 188; POTASSIUM SORBATE; PROPYLENE GLYCOL; WATER; TRISODIUM CITRATE DIHYDRATE; SUCRALOSE

HIGHLIGHTS OF PRESCRIBING INFORMATION

These highlights do not include all the information needed to use PREXXARTANTM safely and effectively. See full prescribing information for PREXXARTANTM.
PREXXARTANTM (valsartan) oral solution
Initial U.S. Approval: 1996

WARNING: FETAL TOXICITY

See full prescribing information for complete boxed warning.

- When pregnancy is detected, discontinue PREXXARTAN as soon as possible. (5.1)
- Drugs that act directly on the renin-angiotensin system can cause injury and death to the developing fetus. (5.1)

1 INDICATIONS AND USAGE

PREXXARTAN is an angiotensin II receptor blocker (ARB) indicated for:

- Hypertension in adults and children six years and older, to lower blood pressure. Lowering blood pressure reduces the risk of fatal and nonfatal cardiovascular events, primarily strokes and myocardial infarctions (1.1)
- Heart failure (NYHA class II-IV); PREXXARTAN significantly reduces hospitalization for heart failure in patients who are unable to swallow valsartan tablets (1.2)
- Stable left ventricular failure or left ventricular dysfunction following myocardial infarction; PREXXARTAN reduces cardiovascular mortality in patients who are unable to swallow valsartan tablets (1.3)

2 DOSAGE AND ADMINISTRATION

Indication | Starting Dose | Dose Range | Target Maintenance Dose*
Hypertension - adults(2.1) | 40 or 80 mg twice daily | 40 -160 mg twice daily | ---
Hypertension—age 6 to16 years (2.2) | 0.65 mg/kg twice daily (up to 40 mg total) | 0.65-1.35 mg/kg twice daily (up to 40 mg-160 mg total) | ---
Heart Failure (2.3) | 40 mg twice daily | 40 mg-160 mg twice daily | 160 mg twice daily
Post-Myocardial Infarction (2.4) | 20 mg twice daily | 20 mg to 160 mg twice daily | 160 mg twice daily

* as tolerated by patient

3 DOSAGE FORMS AND STRENGTHS

Oral Solution, 4 mg/mL

4 CONTRAINDICATIONS

Known hypersensitivity (4)
Patients with diabetes on aliskiren (4)

5 WARNINGS AND PRECAUTIONS

- Observe for signs and symptoms of hypotension (5.2)
- Monitor renal function and potassium in susceptible patients (5.3, 5.4)

6 ADVERSE REACTIONS

Hypertension: Most common adverse reactions are headache, dizziness, fatigue and abdominal pain (6.1)
Heart Failure: Most common adverse reactions are dizziness, hypotension, diarrhea, arthralgia, back pain, fatigue and hyperkalemia (6.1)
Post-Myocardial Infarction: Most common adverse reactions which caused patients to discontinue therapy are hypotension, cough and increased blood creatinine (6.1)

To report SUSPECTED ADVERSE REACTIONS, contact Medicure at 1-800-509-0544 or FDA at 1-800-FDA-1088 or www.fda.gov/medwatch.

7 DRUG INTERACTIONS

- Potassium-sparing diuretics, potassium supplements or salt substitutes may lead to increases in serum potassium, and in heart failure patients, increases in serum creatinine (7)
- NSAIDs increase risk of renal impairment and loss of antihypertensive effect (7)
- Dual inhibition of the renin-angiotensin system: Increased risk of renal impairment, hypotension, and hyperkalemia (7)
- Lithium: Increases in serum lithium concentrations and lithium toxicity (7)

8 USE IN SPECIFIC POPULATIONS

Lactation: Breastfeeding not recommended. (8.2).
Pediatrics: Efficacy and safety data support use in 6-16 year old patients; use is not recommended in patients <6 years old (6.1, 8.4)

FULL PRESCRIBING INFORMATION

WARNING: FETAL TOXICITY

- When pregnancy is detected, discontinue PREXXARTAN as soon as possible. (5.1)
- Drugs that act directly on the renin-angiotensin system can cause injury and death to the developing fetus. (5.1)

1 INDICATIONS AND USAGE

1.1 Hypertension

PREXXARTAN is indicated for the treatment of hypertension in adults and children six years and older, to lower blood pressure. Lowering blood pressure reduces the risk of fatal and nonfatal cardiovascular events, primarily strokes and myocardial infarctions. These benefits have been seen in controlled trials of antihypertensive drugs from a wide variety of pharmacologic classes including the class to which valsartan principally belongs. There are no controlled trials in hypertensive patients demonstrating risk reduction with valsartan.

Control of high blood pressure should be part of comprehensive cardiovascular risk management, including, as appropriate, lipid control, diabetes management, antithrombotic therapy, smoking cessation, exercise, and limited sodium intake. Many patients will require more than one drug to achieve blood pressure goals. For specific advice on goals and management, see published guidelines, such as those of the National High Blood Pressure Education Program’s Joint National Committee on Prevention, Detection, Evaluation, and Treatment of High Blood Pressure (JNC).

Numerous antihypertensive drugs, from a variety of pharmacologic classes and with different mechanisms of action, have been shown in randomized controlled trials to reduce cardiovascular morbidity and mortality, and it can be concluded that it is blood pressure reduction, and not some other pharmacologic property of the drugs, that is largely responsible for those benefits. The largest and most consistent cardiovascular outcome benefit has been a reduction in the risk of stroke, but reductions in myocardial infarction and cardiovascular mortality also have been seen regularly.

Elevated systolic or diastolic pressure causes increased cardiovascular risk, and the absolute risk increase per mmHg is greater at higher blood pressures, so that even modest reductions of severe hypertension can provide substantial benefit. Relative risk reduction from blood pressure reduction is similar across populations with varying absolute risk, so the absolute benefit is greater in patients who are at higher risk independent of their hypertension (e.g., patients with diabetes or hyperlipidemia), and such patients would be expected to benefit from more aggressive treatment to a lower blood pressure goal.

Some antihypertensive drugs have smaller blood pressure effects (as monotherapy) in black patients, and many antihypertensive drugs have additional approved indications and effects (e.g., on angina, heart failure, or diabetic kidney disease). These considerations may guide selection of therapy.

PREXXARTAN may be used alone or in combination with other antihypertensive agents.

1.2 Heart Failure

PREXXARTAN is indicated for the treatment of heart failure (NYHA class II-IV) to reduce the risk of hospitalization for heart failure in patients who are unable to swallow valsartan tablets. There is no evidence that valsartan provides added benefits when it is used with an adequate dose of an ACE inhibitor [see Warnings and Precautions (5.2), Clinical Pharmacology (12.3) and Clinical Studies (14.2)].

1.3 Post-Myocardial Infarction

PREXXARTAN is indicated to reduce the risk of cardiovascular death in clinically stable patients with left ventricular failure or left ventricular dysfunction following myocardial infarction who are unable to swallow valsartan tablets [see Warnings and Precautions (5.2), Clinical Pharmacology (12.3) and Clinical Studies (14.3)].

2 DOSAGE AND ADMINISTRATION

2.1 General Considerations

PREXXARTAN is not therapeutically equivalent to the tablet formulation of Diovan. The peak concentration of valsartan with PREXXARTAN is higher than with Diovan [see Warnings and Precautions (5.2), Clinical Pharmacology (12.3)]. Follow dosing instructions given here.

2.2 Adult Hypertension

The recommended starting dose of PREXXARTAN is 40 mg or 80 mg twice daily when used as monotherapy in patients who are not volume-depleted. Patients requiring greater reductions in blood pressure may be started at 80 mg administered twice a day. PREXXARTAN may be used over a total daily dose range of 80 mg to 320 mg.

The antihypertensive effect is substantially present within 2 weeks and maximal reduction is generally attained after 4 weeks. If additional antihypertensive effect is required over the starting dose range, the total daily dose may be increased to a maximum of 320 mg or a diuretic may be added. Addition of a diuretic has a greater effect than dose increases beyond 80 mg.

No initial dosage adjustment is required for elderly patients, for patients with mild or moderate renal impairment, or for patients with mild or moderate liver insufficiency. Monitor closely patients with severe hepatic or renal impairment.

PREXXARTAN may be administered with other antihypertensive agents.

2.3 Pediatric Hypertension 6 to 16 Years of Age

The recommended starting dose is 0.65 mg/kg twice daily (up to 40 mg total daily dose). The dosage should be adjusted according to blood pressure response. Doses higher than 1.35 mg/kg twice daily (or >160 mg total daily dose) have not been studied in pediatric patients 6 to 16 years old.

No data are available in pediatric patients either undergoing dialysis or with a glomerular filtration rate <30 mL/min/1.73 m^2 [see Use in Specific Populations (8.4)].

PREXXARTAN is not recommended for patients under 6 years of age [see Adverse Reactions (6.1), Use in Specific Populations (8.4), Clinical Studies (14.1)].

2.4 Heart Failure

The recommended starting dose of PREXXARTAN is 40 mg twice daily. Titrate to 80 mg and 160 mg twice daily, as tolerated by the patient. Consider reducing the dose of concomitant diuretics. The maximum daily dose administered in clinical trials is 320 mg in divided doses.

2.5 Post-Myocardial Infarction

PREXXARTAN may be initiated as early as 12 hours after a myocardial infarction. The recommended starting dose of PREXXARTAN is 20 mg twice daily. Patients may be up titrated within 7 days to 40 mg twice daily, with subsequent titrations to a target maintenance dose of 160 mg twice daily, as tolerated by the patient. If symptomatic hypotension or renal dysfunction occurs, consider dosage reduction. PREXXARTAN may be given with other standard post-myocardial infarction treatment, including thrombolytics, aspirin, beta-blockers, and statins.

3 DOSAGE FORMS AND STRENGTHS

4 mg/mL aqueous solution.

4 CONTRAINDICATIONS

Do not use in patients with known hypersensitivity to any component.
Do not coadminister aliskiren with PREXXARTAN in patients with diabetes [see Drug Interactions (7)].

5 WARNINGS AND PRECAUTIONS

5.1 Fetal Toxicity

Use of drugs that act on the renin-angiotensin system during the second and third trimesters of pregnancy reduces fetal renal function and increases fetal and neonatal morbidity and death. Resulting oligohydramnios can be associated with fetal lung hypoplasia and skeletal deformations. Potential neonatal adverse effects include skull hypoplasia, anuria, hypotension, renal failure, and death. When pregnancy is detected, discontinue PREXXARTAN as soon as possible [see Use in Specific Populations (8.1)].

5.2 Hypotension

In patients with an activated renin-angiotensin system, such as volume- and/or salt-depleted patients receiving high doses of diuretics, symptomatic hypotension may occur. This condition should be corrected prior to administration of valsartan, or the treatment should start under close medical supervision.

Peak plasma concentrations of valsartan are higher following administration of PREXXARTAN and may result in increased risk of hypotension as compared to administration of valsartan tablets [see Clinical Pharmacology (12.3)]. Patients with heart failure or post-myocardial infarction patients given valsartan tablets in clinical trials commonly had some reduction in blood pressure. Only use PREXXARTAN in heart failure or post-myocardial infarction patients who are unable to swallow valsartan tablets. In clinical trials of valsartan tablets, discontinuation of therapy because of continuing symptomatic hypotension usually was not necessary. In controlled trials in heart failure patients, the incidence of hypotension in valsartan-treated patients was 5.5% compared to 1.8% in placebo-treated patients. In the Valsartan in Acute Myocardial Infarction Trial (VALIANT), hypotension in post-myocardial infarction patients led to permanent discontinuation of therapy in 1.4% of valsartan-treated patients and 0.8% of captopril-treated patients.

If symptomatic hypotension occurs, place the patient in the supine position and, if necessary, give an intravenous infusion of normal saline. A transient hypotensive response is not a contraindication to further treatment, which usually can be continued without difficulty once the blood pressure has stabilized.

5.3 Impaired Renal Function

Changes in renal function including acute renal failure can be caused by drugs that inhibit the renin-angiotensin system and by diuretics. Patients whose renal function may depend in part on the activity of the renin-angiotensin system (e.g., patients with renal artery stenosis, chronic kidney disease, severe congestive heart failure, or volume depletion) may be at particular risk of developing acute renal failure on valsartan. Monitor renal function periodically in these patients. Consider withholding or discontinuing therapy in patients who develop a clinically significant decrease in renal function on valsartan [see Drug Interactions (7)].

5.4 Hyperkalemia

Some patients with heart failure have developed increases in potassium. These effects are usually minor and transient, and they are more likely to occur in patients with pre-existing renal impairment. Dosage reduction and/or discontinuation of PREXXARTAN may be required [see Adverse Reactions (6.1)].

6 ADVERSE REACTIONS

6.1 Clinical Studies Experience

Because clinical studies are conducted under widely varying conditions, adverse reaction rates observed in the clinical studies of a drug cannot be directly compared to rates in the clinical studies of another drug and may not reflect the rates observed in practice.

Adult Hypertension

Valsartan has been evaluated for safety in more than 4,000 patients, including over 400 treated for over 6 months, and more than 160 for over 1 year. Adverse reactions have generally been mild and transient in nature and have only infrequently required discontinuation of therapy. The overall incidence of adverse reactions with valsartan was similar to placebo.
The overall frequency of adverse reactions was neither dose-related nor related to gender, age, race, or regimen. Discontinuation of therapy due to side effects was required in 2.3% of valsartan patients and 2.0% of placebo patients. The most common reasons for discontinuation of therapy with valsartan were headache and dizziness.
The adverse reactions that occurred in placebo-controlled clinical trials in at least 1% of patients treated with valsartan and at a higher incidence in valsartan (n=2,316) than placebo (n=888) patients included fatigue (2% vs. 1%) and abdominal pain (2% vs. 1%).
Headache, dizziness, upper respiratory infection, cough, diarrhea, rhinitis, sinusitis, nausea, pharyngitis, edema, and arthralgia occurred at a more than 1% rate, but at about the same incidence in placebo and valsartan patients.
In trials in which valsartan was compared to an ACE inhibitor with or without placebo, the incidence of dry cough was significantly greater in the ACE-inhibitor group (7.9%) than in the groups who received valsartan (2.6%) or placebo (1.5%). In a 129-patient trial limited to patients who had dry cough when they had previously received ACE inhibitors, the incidences of cough in patients who received valsartan, HCTZ, or lisinopril were 20%, 19%, and 69% respectively (p <0.001).
Dose-related orthostatic effects were seen in less than 1% of patients. An increase in the incidence of dizziness was observed in patients treated with valsartan 320 mg (8%) compared to 10 to 160 mg (2% to 4%).
Valsartan has been used concomitantly with hydrochlorothiazide without evidence of clinically important adverse interactions.
Other adverse reactions that occurred in controlled clinical trials of patients treated with valsartan (>0.2% of valsartan patients) are listed below. It cannot be determined whether these events were causally related to valsartan.

Body as a Whole: Allergic reaction and asthenia

Cardiovascular: Palpitations

Dermatologic: Pruritus and rash

Digestive: Constipation, dry mouth, dyspepsia, and flatulence

Musculoskeletal: Back pain, muscle cramps, and myalgia

Neurologic and Psychiatric: Anxiety, insomnia, paresthesia, and somnolence

Respiratory: Dyspnea

Special Senses: Vertigo

Urogenital: Impotence

Other reported events seen less frequently in clinical trials included chest pain, syncope, anorexia, vomiting, and angioedema.

Pediatric Hypertension

Valsartan has been evaluated for safety in over 400 pediatric patients aged 6 to 17 years and more than 160 pediatric patients aged 6 months to 5 years. No relevant differences were identified between the adverse experience profile for pediatric patients aged 6 to 16 years and that previously reported for adult patients. Headache and hyperkalemia were the most common adverse events suspected to be study drug-related in older children (6 to 17 years old) and younger children (6 months to 5 years old), respectively. Hyperkalemia was mainly observed in children with underlying renal disease.

Neurocognitive and developmental assessment of pediatric patients aged 6 to 16 years revealed no overall clinically relevant adverse impact after treatment with valsartan for up to 1 year.

Valsartan is not recommended for pediatric patients under 6 years of age. In a study (n=90) of pediatric patients (1 to 5 years), two deaths and three cases of on-treatment transaminase elevations were seen in the one-year open-label extension phase. These 5 events occurred in a study population in which patients frequently had significant co-morbidities. A causal relationship to valsartan has not been established. In a second study of 6-months duration in 75 children aged 1 to 5 years, there were no deaths; one case of marked liver transaminase elevations occurred following 6 months of treatment.

Heart Failure

The adverse experience profile of valsartan in heart failure patients was consistent with the pharmacology of the drug and the health status of the patients. In the Valsartan Heart Failure Trial, comparing valsartan in total daily doses up to 320 mg (n=2,506) to placebo (n=2,494), 10% of valsartan patients discontinued for adverse reactions vs. 7% of placebo patients.

The table shows adverse reactions in double-blind short-term heart failure trials, including the first 4 months of the Valsartan Heart Failure Trial, with an incidence of at least 2% that were more frequent in valsartan-treated patients than in placebo-treated patients. All patients received standard drug therapy for heart failure, frequently as multiple medications, which could include diuretics, digitalis, beta-blockers. About 93% of patients received concomitant ACE inhibitors.

 | Valsartan (n=3,282) | Placebo (n=2,740)
Dizziness | 17% | 9%
Hypotension | 7% | 2%
Diarrhea | 5% | 4%
Arthralgia | 3% | 2%
Fatigue | 3% | 2%
Back Pain | 3% | 2%
Dizziness, postural | 2% | 1%
Hyperkalemia | 2% | 1%
Hypotension, postural | 2% | 1%

Discontinuations occurred in 0.5% of valsartan-treated patients and 0.1% of placebo patients for each of the following: elevations in creatinine and elevations in potassium.

Other adverse reactions with an incidence greater than 1% and greater than placebo included headache, nausea, renal impairment, syncope, blurred vision, upper abdominal pain and vertigo.

From the long-term data in the Valsartan Heart Failure Trial, there did not appear to be any significant adverse reactions not previously identified.

Post-Myocardial Infarction

The safety profile of valsartan was consistent with the pharmacology of the drug and the background diseases, cardiovascular risk factors, and clinical course of patients treated in the post-myocardial infarction setting. The table shows the percentage of patients discontinued in the valsartan and captopril-treated groups in the Valsartan in Acute Myocardial Infarction Trial (VALIANT) with a rate of at least 0.5% in either of the treatment groups.

Discontinuations due to renal dysfunction occurred in 1.1% of valsartan-treated patients and 0.8% of captopril-treated patients.

 | Valsartan (n=4,885) | Captopril (n=4,879)
Discontinuation for adverse reaction | 5.8% | 7.7%
Adverse reactions
Hypotension NOS | 1.4% | 0.8%
Cough | 0.6% | 2.5%
Blood creatinine increased | 0.6% | 0.4%
Rash NOS | 0.2% | 0.6%

In controlled clinical trials, clinically important changes in standard laboratory parameters were rarely associated with administration of valsartan.

Creatinine: Minor elevations in creatinine occurred in 0.8% of patients taking valsartan and 0.6% given placebo in controlled clinical trials of hypertensive patients. In heart failure trials, greater than 50% increases in creatinine were observed in 3.9% of valsartan-treated patients compared to 0.9% of placebo-treated patients. In post-myocardial infarction patients, doubling of serum creatinine was observed in 4.2% of valsartan-treated patients and 3.4% of captopril-treated patients.

Hemoglobin and Hematocrit: Greater than 20% decreases in hemoglobin and hematocrit were observed in 0.4% and 0.8%, respectively, of valsartan patients, compared with 0.1% and 0.1% in placebo-treated patients.

Liver Function Tests: Occasional elevations (greater than 150%) of liver chemistries occurred in valsartan-treated patients. Three patients (<0.1%) treated with valsartan discontinued treatment for elevated liver chemistries.

Neutropenia: Neutropenia was observed in 1.9% of patients treated with valsartan and 0.8% of patients treated with placebo.

Serum Potassium: In hypertensive patients, greater than 20% increases in serum potassium were observed in 4.4% of valsartan-treated patients compared to 2.9% of placebo-treated patients. In heart failure patients, greater than 20% increases in serum potassium were observed in 10.0% of valsartan-treated patients compared to 5.1% of placebo-treated patients.

Blood Urea Nitrogen (BUN): In heart failure trials, greater than 50% increases in BUN were observed in 16.6% of valsartan-treated patients compared to 6.3% of placebo-treated patients.

6.2 Postmarketing Experience

The following additional adverse reactions have been reported in postmarketing experience:

Hypersensitivity: There are rare reports of angioedema. Some of these patients previously experienced angioedema with other drugs including ACE inhibitors. Valsartan should not be re-administered to patients who have had angioedema.
Digestive: Elevated liver enzymes and very rare reports of hepatitis
Renal: Impaired renal function, renal failure
Clinical Laboratory Tests: Hyperkalemia
Dermatologic: Alopecia, bullous dermatitis
Blood and Lymphatic: There are very rare reports of thrombocytopenia
Vascular: Vasculitis

Rare cases of rhabdomyolysis have been reported in patients receiving angiotensin II receptor blockers.

Because these reactions are reported voluntarily from a population of uncertain size, it is not possible to estimate their frequency reliably or establish a causal relationship to drug exposure.

7 DRUG INTERACTIONS

7.1 Agents Increasing Serum Potassium

Concomitant use of valsartan with other agents that block the renin-angiotensin system, potassium-sparing diuretics (e.g., spironolactone, triamterene, amiloride), potassium supplements, salt substitutes containing potassium or other drugs that may increase potassium levels (e.g., heparin) may lead to increases in serum potassium and in heart failure patients to increases in serum creatinine. If co-medication is considered necessary, monitor serum potassium.

7.2 Non-Steroidal Anti-Inflammatory Agents including Selective Cyclooxygenase-2 Inhibitors (COX-2 Inhibitors)

In patients who are elderly, volume-depleted (including those on diuretic therapy), or with compromised renal function, coadministration of NSAIDs, including selective COX-2 inhibitors, with angiotensin II receptor antagonists, including valsartan, may result in deterioration of renal function, including possible acute renal failure. These effects are usually reversible. Monitor renal function periodically in patients receiving valsartan and NSAID therapy.

The antihypertensive effect of angiotensin II receptor antagonists, including valsartan, may be attenuated by NSAIDs including selective COX-2 inhibitors.

7.3 Dual Blockade of the Renin-Angiotensin System (RAS)

Dual blockade of the RAS with angiotensin receptor blockers, ACE inhibitors, or aliskiren is associated with increased risks of hypotension, hyperkalemia, and changes in renal function (including acute renal failure) compared to monotherapy. Most patients receiving the combination of two RAS inhibitors do not obtain any additional benefit compared to monotherapy. In general, avoid combined use of RAS inhibitors. Closely monitor blood pressure, renal function and electrolytes in patients on PREXXARTAN and other agents that affect the RAS.

Do not coadminister aliskiren with PREXXARTAN in patients with diabetes. Avoid use of aliskiren with PREXXARTAN in patients with renal impairment (GFR < 60 mL/min).

7.4 Lithium

Increases in serum lithium concentrations and lithium toxicity have been reported during concomitant administration of lithium with angiotensin II receptor antagonists, including valsartan. Monitor serum lithium levels during concomitant use.

8 USE IN SPECIFIC POPULATIONS

8.1 Pregnancy

Risk Summary
PREXXARTAN can cause fetal harm when administered to a pregnant woman. Use of drugs that act on the renin-angiotensin system during the second and third trimesters of pregnancy reduces fetal renal function and increases fetal and neonatal morbidity and death. Most epidemiologic studies examining fetal abnormalities after exposure to antihypertensive use in the first trimester have not distinguished drugs affecting the renin-angiotensin system from other antihypertensive agents. Published reports include cases of anhydramnios and oligohydramnios in pregnant women treated with valsartan (see Clinical Considerations). Studies in rats and rabbits with valsartan showed fetotoxicity only at maternally toxic doses (see Data). When pregnancy is detected, discontinue PREXXARTAN as soon as possible.

The estimated background risk of major birth defects and miscarriage for the indicated population is unknown. All pregnancies have a background risk of birth defect, loss, or other adverse outcomes. In the U.S. general population, the estimated background risk of major malformations and miscarriage in clinically recognized pregnancies is 2-4%, and 15-20%, respectively.

Clinical Considerations
Disease-associated maternal and/or embryo/fetal risk
Hypertension in pregnancy increases the maternal risk for pre-eclampsia, gestational diabetes, premature delivery, and delivery complications (e.g., need for cesarean section, and post-partum hemorrhage). Hypertension increases the fetal risk for intrauterine growth restriction and intrauterine death. Pregnant women with hypertension should be carefully monitored and managed accordingly.

Fetal/Neonatal adverse reactions
Oligohydramnios in pregnant women who use drugs affecting the renin-angiotensin system in the second and third trimesters of pregnancy can result in the following: reduced fetal renal function leading to anuria and renal failure, fetal lung hypoplasia and skeletal deformations, including skull hypoplasia, hypotension, and death. In the unusual case that there is no appropriate alternative to therapy with drugs affecting the renin-angiotensin system for a particular patient, apprise the mother of the potential risk to the fetus.

In patients taking PREXXARTAN during pregnancy, perform serial ultrasound examinations to assess the intra-amniotic environment. Fetal testing may be appropriate, based on the week of gestation. Patients and physicians should be aware, however, that oligohydramnios may not appear until after the fetus has sustained irreversible injury. Closely observe infants with histories of in utero exposure to PREXXARTAN for hypotension, oliguria, and hyperkalemia. If oliguria or hypotension occur in neonates with a history of in utero exposure to PREXXARTAN, support blood pressure and renal perfusion. Exchange transfusions or dialysis may be required as a means of reversing hypotension and substituting for disordered renal function.

Data
Animal Data
No teratogenic effects were observed when valsartan was administered to pregnant mice and rats at oral doses up to 600 mg/kg/day and to pregnant rabbits at oral doses up to 10 mg/kg/day. However, significant decreases in fetal weight, pup birth weight, pup survival rate, and slight delays in developmental milestones were observed in studies in which parental rats were treated with valsartan at oral, maternally toxic (reduction in body weight gain and food consumption) doses of 600 mg/kg/day during organogenesis or late gestation and lactation. In rabbits, fetotoxicity (i.e., resorptions, litter loss, abortions, and low body weight) associated with maternal toxicity (mortality) was observed at doses of 5 and 10 mg/kg/day. The no observed adverse effect doses of 600, 200 and 2 mg/kg/day in mice, rats and rabbits represent 9, 6, and 0.1 times, respectively, the maximum recommended human dose on a mg/m^2 basis. Calculations assume an oral dose of 320 mg/day and a 60-kg patient.

8.2 Lactation

Risk Summary
There are no data on the presence of PREXXARTAN in human milk, the effects on the breastfed infant, or the effects on milk production. Valsartan is present in rat milk (see Data). Because of the potential for valsartan to affect postnatal renal development in nursing infants, advise a nursing woman not to breastfeed during treatment with PREXXARTAN.

Data
Valsartan was detected in the milk of lactating rats 15 minutes after administration of a 3 mg/kg dose.

8.4 Pediatric Use

Valsartan is not recommended for pediatric patients under 6 years of age due to safety findings for which a relationship to treatment could not be excluded [see Adverse Reactions (6.1)]. Furthermore, it is unknown whether post-natal use of valsartan before maturation of renal function is complete has long-term deleterious effects on the kidney. In humans, nephrogenesis is thought to be complete around birth; however, maturation of other aspects of kidney function (such as glomerular filtration and tubular function) may continue until approximately 2 years of age.

The antihypertensive effects of valsartan have been evaluated in two randomized, double-blind clinical studies in pediatric patients from 1-5 and 6-16 years of age [see Clinical Studies (14.1)]. The pharmacokinetics of valsartan have been evaluated in pediatric patients 1 to 16 years of age [see Clinical Pharmacology (12.3)]. Valsartan was generally well tolerated in children 6-16 years and the adverse experience profile was similar to that described for adults.
In children and adolescents with hypertension where underlying renal abnormalities may be more common, renal function and serum potassium should be closely monitored as clinically indicated.

No data are available in pediatric patients either undergoing dialysis or with a glomerular filtration rate <30 mL/min/1.73 m^2.
There is limited clinical experience with valsartan in pediatric patients with mild to moderate hepatic impairment [see Warnings and Precautions (5.3)].

8.5 Geriatric Use

In the controlled clinical trials of valsartan, 1,214 (36.2%) hypertensive patients treated with valsartan were ≥65 years and 265 (7.9%) were ≥75 years. No overall difference in the efficacy or safety of valsartan was observed in this patient population, but greater sensitivity of some older individuals cannot be ruled out.

Of the 2,511 patients with heart failure randomized to valsartan in the Valsartan Heart Failure Trial, 45% (1,141) were 65 years of age or older. In the Valsartan in Acute Myocardial Infarction Trial (VALIANT), 53% (2,596) of the 4,909 patients treated with valsartan and 51% (2,515) of the 4,885 patients treated with valsartan + captopril were 65 years of age or older. There were no notable differences in efficacy or safety between older and younger patients in either trial.

8.6 Renal Impairment

Safety and effectiveness of valsartan in patients with severe renal impairment (CrCl ≤ 30 mL/min) have not been established. No dose adjustment is required in patients with mild (CrCl 60 to 90 mL/min) or moderate (CrCl 30 to 60 mL/min) renal impairment.

8.7 Hepatic Impairment

No dose adjustment is necessary for patients with mild-to-moderate liver disease. No dosing recommendations can be provided for patients with severe liver disease.

10 OVERDOSAGE

Limited data are available related to overdosage in humans. The most likely manifestations of overdosage would be hypotension and tachycardia; bradycardia could occur from parasympathetic (vagal) stimulation. Depressed level of consciousness, circulatory collapse and shock have been reported. If symptomatic hypotension should occur, supportive treatment should be instituted.
Valsartan is not removed from the plasma by hemodialysis.
Valsartan was without grossly observable adverse effects at single oral doses up to 2000 mg/kg in rats and up to 1000 mg/kg in marmosets, except for salivation and diarrhea in the rat and vomiting in the marmoset at the highest dose (60 and 31 times, respectively, the maximum recommended human dose on a mg/m^2 basis). (Calculations assume an oral dose of 320 mg/day and a 60-kg patient.)

11 DESCRIPTION

PREXXARTAN (valsartan) is a nonpeptide, orally active, and specific angiotensin II receptor blocker acting on the AT1 receptor subtype.

Valsartan is chemically described as N-(1-oxopentyl)-N-[[2′-(1H-tetrazol-5-yl) [1,1′-biphenyl]-4-yl]methyl]-L-valine. Its empirical formula is C24H29N5O3, its molecular weight is 435.5, and its structural formula is:

Valsartan is a white to practically white fine powder. It is soluble in ethanol and methanol and slightly soluble in water.

PREXXARTAN is formulated at a concentration of 4 mg/mL valsartan in a grape flavored aqueous solution for oral administration. The inactive ingredients are: grape flavor, methylparaben NF, poloxamer 188, potassium sorbate, propylene glycol NF, purified water USP, sodium citrate dihydrate USP, and sucralose NF.

12 CLINICAL PHARMACOLOGY

12.1 Mechanism of Action

Angiotensin II is formed from angiotensin I in a reaction catalyzed by angiotensin-converting enzyme (ACE, kininase II). Angiotensin II is the principal pressor agent of the renin-angiotensin system, with effects that include vasoconstriction, stimulation of synthesis and release of aldosterone, cardiac stimulation, and renal reabsorption of sodium. Valsartan blocks the vasoconstrictor and aldosterone-secreting effects of angiotensin II by selectively blocking the binding of angiotensin II to the AT1 receptor in many tissues, such as vascular smooth muscle and the adrenal gland. Its action is therefore independent of the pathways for angiotensin II synthesis.
There is also an AT2 receptor found in many tissues, but AT2 is not known to be associated with cardiovascular homeostasis. Valsartan has much greater affinity (about 20,000-fold) for the AT1 receptor than for the AT2 receptor. The increased plasma levels of angiotensin II following AT1 receptor blockade with valsartan may stimulate the unblocked AT2 receptor. The primary metabolite of valsartan is essentially inactive with an affinity for the AT1 receptor about one-200th that of valsartan itself.

Blockade of the renin-angiotensin system with ACE inhibitors, which inhibit the biosynthesis of angiotensin II from angiotensin I, is widely used in the treatment of hypertension. ACE inhibitors also inhibit the degradation of bradykinin, a reaction also catalyzed by ACE. Because valsartan does not inhibit ACE (kininase II), it does not affect the response to bradykinin. Whether this difference has clinical relevance is not yet known. Valsartan does not bind to or block other hormone receptors or ion channels known to be important in cardiovascular regulation.

Blockade of the angiotensin II receptor inhibits the negative regulatory feedback of angiotensin II on renin secretion, but the resulting increased plasma renin activity and angiotensin II circulating levels do not overcome the effect of valsartan on blood pressure.

12.2 Pharmacodynamics

Valsartan inhibits the pressor effect of angiotensin II infusions. An oral dose of 80 mg inhibits the pressor effect by about 80% at peak with approximately 30% inhibition persisting for 24 hours. No information on the effect of larger doses is available.

Removal of the negative feedback of angiotensin II causes a 2- to 3-fold rise in plasma renin and consequent rise in angiotensin II plasma concentration in hypertensive patients. Minimal decreases in plasma aldosterone were observed after administration of valsartan; very little effect on serum potassium was observed.

In multiple-dose studies in hypertensive patients with stable renal insufficiency and patients with renovascular hypertension, valsartan had no clinically significant effects on glomerular filtration rate, filtration fraction, creatinine clearance, or renal plasma flow.

In multiple-dose studies in hypertensive patients, valsartan had no notable effects on total cholesterol, fasting triglycerides, fasting serum glucose, or uric acid.

12.3 Pharmacokinetics

For an equivalent dose, PREXXARTAN has 86% higher peak concentration (Cmax) and 25% higher area under the plasma concentration over time curve (AUC) for valsartan compared to Diovan. AUC and Cmax of valsartan increase approximately linearly with increasing dose over the clinical dosing range. Valsartan does not accumulate appreciably in plasma following repeated administration.

Absorption
PREXXARTAN Cmax is achieved 0.7 to 3.7 hours after dosing.
Effect of Food
High-fat, high-calorie meal decreased the AUC of PREXXARTAN by about 8% and Cmax by about 44%.

Distribution
The steady state volume of distribution of valsartan after intravenous administration is small (17 L), indicating that valsartan does not distribute into tissues extensively. Valsartan is highly bound to serum proteins (95%), mainly serum albumin.

Elimination
Following intravenous administration, plasma clearance of valsartan is about 2 L/h. Renal clearance of valsartan is 0.62 L/h (about 30% of total body clearance). Valsartan shows bi-exponential decay kinetics following intravenous administration, with an average elimination half-life of about 6 hours.

Metabolism
The primary metabolite, accounting for about 9% of dose, is valeryl 4-hydroxy valsartan. In vitro metabolism studies involving recombinant CYP 450 enzymes indicated that the CYP 2C9 isoenzyme is responsible for the formation of valeryl-4-hydroxy valsartan. Valsartan does not inhibit CYP 450 isozymes at clinically relevant concentrations. CYP 450 mediated drug interaction between valsartan and co-administered drugs are unlikely because of the low extent of metabolism.

Excretion
When administered as an oral solution, 83% of the dose is recovered in feces and about 13% is recovered in urine. The recovery is mainly as unchanged drug, with only about 20% of dose recovered as metabolites.

Special Populations:

Geriatric Patients: Exposure (measured by AUC) to valsartan is higher by 70% and the half-life is longer by 35% in the elderly than in the young.

Pediatric Patients: In a study of pediatric hypertensive patients (n=26, 1 to 16 years of age) given single doses of a suspension of valsartan (mean: 0.9 to 2 mg/kg), the clearance (L/h/kg) of valsartan for children was similar to that of adults receiving the same formulation.

Male and Female Patients: Pharmacokinetics of valsartan does not differ significantly between males and females.

Heart Failure Patients: The average time to peak concentration and elimination half-life of valsartan in heart failure patients are similar to those observed in healthy volunteers. AUC and Cmax values of valsartan increase linearly and are almost proportional with increasing dose over the clinical dosing range (40 to 160 mg twice a day). The average accumulation factor is about 1.7. The apparent clearance of valsartan following oral administration is approximately 4.5 L/h. Age does not affect the apparent clearance in heart failure patients.

Patients with Renal Impairment: There is no apparent correlation between renal function (measured by creatinine clearance) and exposure (measured by AUC) to valsartan in patients with different degrees of renal impairment. Consequently, dose adjustment is not required in patients with mild-to-moderate renal dysfunction. No studies have been performed in patients with severe impairment of renal function (creatinine clearance <10 mL/min). Valsartan is not removed from the plasma by hemodialysis. In the case of severe renal disease, monitor closely [see Dosage and Administration (2.1)].

Patients with Hepatic Impairment: On average, patients with mild-to-moderate chronic liver disease have twice the exposure (measured by AUC values) to valsartan of healthy volunteers (matched by age, sex, and weight). In general, no dosage adjustment is needed in patients with mild-to-moderate liver disease. Monitor closely patients with liver disease [see Dosage and Administration (2.1)].

Drug Interactions
No clinically significant pharmacokinetic interactions were observed when valsartan was coadministered with nebivolol, amlodipine, atenolol, cimetidine, digoxin, furosemide, glyburide, hydrochlorothiazide, or indomethacin.
Co-administration of valsartan and warfarin did not change the pharmacokinetics of valsartan or the time-course of the anticoagulant properties of warfarin.

Transporters: The results from an in vitro study with human liver tissue indicate that valsartan is a substrate of the hepatic uptake transporter OATP1B1 and the hepatic efflux transporter MRP2. Coadministration of inhibitors of the uptake transporter (rifampin, cyclosporine) or efflux transporter (ritonavir) may increase the systemic exposure to valsartan.

13 NONCLINICAL TOXICOLOGY

13.1 Carcinogenesis, Mutagenesis, Impairment of Fertility

There was no evidence of carcinogenicity when valsartan was administered in the diet to mice and rats for up to 2 years at doses up to 160 and 200 mg/kg/day, respectively. These doses in mice and rats are about 2.6 and 6 times, respectively, the maximum recommended human dose on a mg/m^2 basis. (Calculations assume an oral dose of 320 mg/day and a 60-kg patient.)

Mutagenicity assays did not reveal any valsartan-related effects at either the gene or chromosome level. These assays included bacterial mutagenicity tests with Salmonella (Ames) and E. coli; a gene mutation test with Chinese hamster V79 cells; a cytogenetic test with Chinese hamster ovary cells; and a rat micronucleus test.

Valsartan had no adverse effects on the reproductive performance of male or female rats at oral doses up to 200 mg/kg/day. This dose is 6 times the maximum recommended human dose on a mg/m^2 basis. (Calculations assume an oral dose of 320 mg/day and a 60-kg patient.)

13.2 Animal Toxicology and/or Pharmacology

Daily oral dosing of neonatal/juvenile rats with valsartan at doses as low as 1 mg/kg/day (about 10% of the maximum recommended pediatric dose on a mg/m^2 basis) from postnatal day 7 to postnatal day 70 produced persistent, irreversible kidney damage. These kidney effects in neonatal rats represent expected exaggerated pharmacological effects that are observed if rats are treated during the first 13 days of life. .

14 CLINICAL STUDIES

14.1 Hypertension

Studies evaluating the antihypertensive effects of valsartan were conducted with a formulation that is not therapeutically equivalent to PREXXARTAN [see Clinical Pharmacology (12.3)].

Adult Hypertension

The antihypertensive effects of valsartan were demonstrated principally in 7 placebo-controlled, 4- to 12-week trials (1 in patients over 65 years) of dosages from 10 to 320 mg/day in patients with baseline diastolic blood pressures of 95-115 mmHg. The studies allowed comparison of once-daily and twice-daily regimens of 160 mg/day; comparison of peak and trough effects; comparison (in pooled data) of response by gender, age, and race; and evaluation of incremental effects of hydrochlorothiazide.

Administration of valsartan to patients with essential hypertension results in a significant reduction of sitting, supine, and standing systolic and diastolic blood pressure, usually with little or no orthostatic change.

In most patients, after administration of a single oral dose, onset of antihypertensive activity occurs at approximately 2 hours, and maximum reduction of blood pressure is achieved within 6 hours. The antihypertensive effect persists for 24 hours after dosing, but there is a decrease from peak effect at lower doses (40 mg) presumably reflecting loss of inhibition of angiotensin II. At higher doses, however (160 mg), there is little difference in peak and trough effect. During repeated dosing, the reduction in blood pressure with any dose is substantially present within 2 weeks, and maximal reduction is generally attained after 4 weeks. In long-term follow-up studies (without placebo control), the effect of valsartan appeared to be maintained for up to 2 years. The antihypertensive effect is independent of age, gender or race. The latter finding regarding race is based on pooled data and should be viewed with caution, because antihypertensive drugs that affect the renin-angiotensin system (that is, ACE inhibitors and angiotensin-II blockers) have generally been found to be less effective in low-renin hypertensives (frequently blacks) than in high-renin hypertensives (frequently whites). In pooled, randomized, controlled trials of valsartan that included a total of 140 blacks and 830 whites, valsartan and an ACE-inhibitor control were generally at least as effective in blacks as whites. The explanation for this difference from previous findings is unclear.

Abrupt withdrawal of valsartan has not been associated with a rapid increase in blood pressure.

The blood pressure-lowering effect of valsartan and thiazide-type diuretics are approximately additive.

The 7 studies of valsartan monotherapy included over 2,000 patients randomized to various doses of valsartan and about 800 patients randomized to placebo. Doses below 80 mg were not consistently distinguished from those of placebo at trough, but doses of 80, 160 and 320 mg produced dose-related decreases in systolic and diastolic blood pressure, with the difference from placebo of approximately 6-9/3-5 mmHg at 80 to 160 mg and 9/6 mmHg at 320 mg. In a controlled trial the addition of HCTZ to valsartan 80 mg resulted in additional lowering of systolic and diastolic blood pressure by approximately 6/3 and 12/5 mmHg for 12.5 and 25 mg of HCTZ, respectively, compared to valsartan 80 mg alone.

Patients with an inadequate response to 80 mg once daily were titrated to either 160 mg once daily or 80 mg twice daily, which resulted in a comparable response in both groups.

In controlled trials, the antihypertensive effect of once-daily valsartan 80 mg was similar to that of once-daily enalapril 20 mg or once-daily lisinopril 10 mg.
There are no trials of valsartan demonstrating reductions in cardiovascular risk in patients with hypertension, but at least one pharmacologically similar drug has demonstrated such benefits.

There was essentially no change in heart rate in valsartan-treated patients in controlled trials.

Pediatric Hypertension

The antihypertensive effects of valsartan were evaluated in two randomized, double-blind clinical studies.
In a clinical study involving 261 hypertensive pediatric patients 6 to 16 years of age, patients who weighed < 35 kg received 10, 40 or 80 mg of valsartan daily (low, medium and high doses), and patients who weighed ≥ 35 kg received 20, 80, and 160 mg of valsartan daily (low, medium and high doses). Renal and urinary disorders, and essential hypertension with or without obesity were the most common underlying causes of hypertension in children enrolled in this study. At the end of 2 weeks, valsartan reduced both systolic and diastolic blood pressure in a dose-dependent manner. Overall, the three dose levels of valsartan (low, medium and high) significantly reduced systolic blood pressure by -8, -10, -12 mmHg from the baseline, respectively. Patients were re-randomized to either continue receiving the same dose of valsartan or were switched to placebo. In patients who continued to receive the medium and high doses of valsartan, systolic blood pressure at trough was -4 and -7 mmHg lower than patients who received the placebo treatment. In patients receiving the low dose of valsartan, systolic blood pressure at trough was similar to that of patients who received the placebo treatment. Overall, the dose-dependent antihypertensive effect of valsartan was consistent across all the demographic subgroups.
In a clinical study involving 90 hypertensive pediatric patients 1 to 5 years of age with a similar study design, there was some evidence of effectiveness, but safety findings for which a relationship to treatment could not be excluded mitigate against recommending use in this age group [see Adverse Reactions (6.1)].

14.2 Heart Failure

The Valsartan Heart Failure Trial (Val-HeFT) was a multinational, double-blind study in which 5,010 patients with NYHA class II (62%) to IV (2%) heart failure and LVEF <40%, on baseline therapy chosen by their physicians, were randomized to placebo or valsartan (titrated from 40 mg twice daily to the highest tolerated dose or 160 mg twice daily) and followed for a mean of about 2 years. The VAL-HeFT study was conducted with a formulation of valsartan that is not therapeutically equivalent to PREXXARTAN [see Clinical Pharmacology (12.3)]. Although Val-HeFT’s primary goal was to examine the effect of valsartan when added to an ACE inhibitor, about 7% were not receiving an ACE inhibitor. Other background therapy included diuretics (86%), digoxin (67%), and beta-blockers (36%). The population studied was 80% male, 46% 65 years or older and 89% Caucasian. At the end of the trial, patients in the valsartan group had a blood pressure that was 4 mmHg systolic and 2 mmHg diastolic lower than the placebo group. There were two primary end points, both assessed as time to first event: all-cause mortality and heart failure morbidity, the latter defined as all-cause mortality, sudden death with resuscitation, hospitalization for heart failure, and the need for intravenous inotropic or vasodilatory drugs for at least 4 hours. These results are summarized in the following table.

 | Placebo | Valsartan | Hazard Ratio | Nominal
 | (N=2,499) | (N=2,511) | (95% CI*) | p-value
All-cause mortality | 484 | 495 | 1.02 | 0.8
 | (19.4%) | (19.7%) | (0.90-1.15)
HF morbidity | 801 | 723 | 0.87 | 0.009
 | (32.1%) | (28.8%) | (0.79-0.97)
* CI = Confidence Interval

Although the overall morbidity result favored valsartan, this result was largely driven by the 7% of patients not receiving an ACE inhibitor, as shown in the following table.

 | Without ACE Inhibitor |  | With ACE Inhibitor
 | Placebo | Valsartan | Placebo | Valsartan
 | (N=181) | (N=185) | (N=2,318) | (N=2,326)
Events (%) | 77 (42.5%) | 46 (24.9%) | 724 (31.2%) | 677 (29.1%)
Hazard ratio (95% CI) | 0.51 (0.35, 0.73) |  | 0.92 (0.82, 1.02)
p-value | 0.0002 |  | 0.0965

The modest favorable trend in the group receiving an ACE inhibitor was largely driven by the patients receiving less than the recommended dose of ACE inhibitor. Thus, there is little evidence of further clinical benefit when valsartan is added to an adequate dose of ACE inhibitor.

Secondary end points in the subgroup not receiving ACE inhibitors were as follows.

 | Placebo | Valsartan | Hazard Ratio
 | (N=181) | (N=185) | (95% CI)
Components of HF morbidity
All-cause mortality | 49 (27.1%) | 32 (17.3%) | 0.59 (0.37, 0.91)
Sudden death with resuscitation | 2 (1.1%) | 1 (0.5%) | 0.47 (0.04, 5.20)
CHF therapy | 1 (0.6%) | 0 (0.0%) | –
CHF hospitalization | 48 (26.5%) | 24 (13.0%) | 0.43 (0.27, 0.71)
Cardiovascular mortality | 40 (22.1%) | 29 (15.7%) | 0.65 (0.40, 1.05)
Non-fatal morbidity | 49 (27.1%) | 24 (13.0%) | 0.42 (0.26, 0.69)

In patients not receiving an ACE inhibitor, valsartan-treated patients had an increase in ejection fraction and reduction in left ventricular internal diastolic diameter (LVIDD).

Effects were generally consistent across subgroups defined by age and gender for the population of patients not receiving an ACE inhibitor. The number of black patients was small and does not permit a meaningful assessment in this subset of patients.

14.3 Post-Myocardial Infarction

The VALsartan In Acute myocardial iNfarcTion trial (VALIANT) was a randomized, controlled, multinational, double-blind study in 14,703 patients with acute myocardial infarction and either heart failure (signs, symptoms or radiological evidence) or left ventricular systolic dysfunction (ejection fraction ≤40% by radionuclide ventriculography or ≤35% by echocardiography or ventricular contrast angiography). The VALIANT study was conducted with a formulation of valsartan that is not therapeutically equivalent to PREXXARTAN [see Clinical Pharmacology (12.3)]. Patients were randomized within 12 hours to 10 days after the onset of myocardial infarction symptoms to one of three treatment groups: valsartan (titrated from 20 or 40 mg twice daily to the highest tolerated dose up to a maximum of 160 mg twice daily), the ACE inhibitor, captopril (titrated from 6.25 mg three times daily to the highest tolerated dose up to a maximum of 50 mg three times daily), or the combination of valsartan plus captopril. In the combination group, the dose of valsartan was titrated from 20 mg twice daily to the highest tolerated dose up to a maximum of 80 mg twice daily; the dose of captopril was the same as for monotherapy. The population studied was 69% male, 94% Caucasian, and 53% were 65 years of age or older. Baseline therapy included aspirin (91%), beta-blockers (70%), ACE inhibitors (40%), thrombolytics (35%) and statins (34%). The mean treatment duration was 2 years. The mean daily dose of valsartan in the monotherapy group was 217 mg.

The primary endpoint was time to all-cause mortality. Secondary endpoints included (1) time to cardiovascular (CV) mortality, and (2) time to the first event of cardiovascular mortality, reinfarction, or hospitalization for heart failure. The results are summarized in the following table.

 | Valsartan vs. Captopril (N=4,909) (N=4,909) |  |  | Valsartan + Captopril vs. Captopril (N=4,885) (N=4,909)
 | No. of Deaths Valsartan/Captopril | Hazard Ratio CI | p-value | No. of Deaths Comb/Captopril | Hazard Ratio CI | p-value
All-cause mortality | 979 (19.9%) /958 (19.5%) | 1.001 (0.902, 1.111) | 0.98 | 941 (19.3%) /958 (19.5%) | 0.984 (0.886, 1.093) | 0.73
CV mortality | 827 (16.8%) /830 (16.9%) | 0.976 (0.875, 1.090)
CV mortality, hospitalization for HF, and recurrent non-fatal MI | 1,529 (31.1%) /1,567 (31.9%) | 0.955 (0.881, 1.035)

There was no difference in overall mortality among the three treatment groups. There was thus no evidence that combining the ACE inhibitor captopril and the angiotensin II blocker valsartan was of value.

The data were assessed to see whether the effectiveness of valsartan could be demonstrated by showing in a non-inferiority analysis that it preserved a fraction of the effect of captopril, a drug with a demonstrated survival effect in this setting. A conservative estimate of the effect of captopril (based on a pooled analysis of 3 post-infarction studies of captopril and 2 other ACE inhibitors) was a 14% to 16% reduction in mortality compared to placebo. Valsartan would be considered effective if it preserved a meaningful fraction of that effect and unequivocally preserved some of that effect. As shown in the table, the upper bound of the CI for the hazard ratio (valsartan/captopril) for overall or CV mortality is 1.09 to 1.11, a difference of about 9% to 11%, thus making it unlikely that valsartan has less than about half of the estimated effect of captopril and clearly demonstrating an effect of valsartan. The other secondary endpoints were consistent with this conclusion.

Effects on Mortality Amongst Subgroups in VALIANT

There were no clear differences in all-cause mortality based on age, gender, race, or baseline therapies, as shown in the figure above.

16 HOW SUPPLIED/STORAGE AND HANDLING

PREXXARTAN (valsartan) Oral Solution contains 4 mg/mL valsartan for oral administration. PREXXARTAN is packaged in bottles containing 473 mL, bottles containing 120 mL and unit dose cups containing 20 mL.
White HDPE bottles of 473 mL: NDC 25208-100-08
White HDPE bottles of 120 mL: NDC 25208-100-07
Unit Dose Cups of 20 mL: NDC 25208-100-06
Store at 20 °C-25 °C (68 °F-77 °F); excursions permitted to 15 °C -30 °C (59 °F -86 °F) [see USP Controlled Room Temperature].
Dispense in tight container (USP).

17 PATIENT COUNSELING INFORMATION

Fetal Toxicity
Advise pregnant women and females of reproductive potential of the potential risk to a fetus. Advise females of reproductive potential to notify their healthcare provider with a known or suspected pregnancy [see Warnings and Precautions (5.1) and Use in Specific Populations (8.1)].
Lactation
Advise women not to breastfeed during treatment with PREXXARTAN [see Use in Specific Populations (8.2)].
Symptomatic Hypotension
Advise patients that lightheadedness can occur, especially during the first days of therapy, and that it should be reported to the prescribing physician. Tell patients that if syncope occurs to discontinue PREXXARTAN until the physician has been consulted.
Caution all patients that inadequate fluid intake, excessive perspiration, diarrhea, or vomiting can lead to an excessive fall in blood pressure, with the same consequences of lightheadedness and possible syncope.
Hyperkalemia
Advise patients not to use salt substitutes containing potassium without consulting their physician.

Manufactured by:
BioRamo LLC
Ft. Lauderdale, FL 33309 USA

Distributed by:

Somerset, NJ 08873 USA
PIM-PRX-01

PACKAGE LABEL.PRINCIPAL DISPLAY PANEL

NDC 25208-100-07
120 mL
PrexxartanTM
(valsartan) Oral Solution
20 mg/5mL
(4 mg/mL)

120 mL Bottle

NDC 25208-100-08
473 mL
PrexxartanTM
(valsartan) Oral Solution
20 mg/5mL
(4 mg/mL)

473 mL Bottle

NDC 25208-100-06
PrexxartanTM
(valsartan) Oral Solution
80 mg in 20 mL

Unit Dose Cup